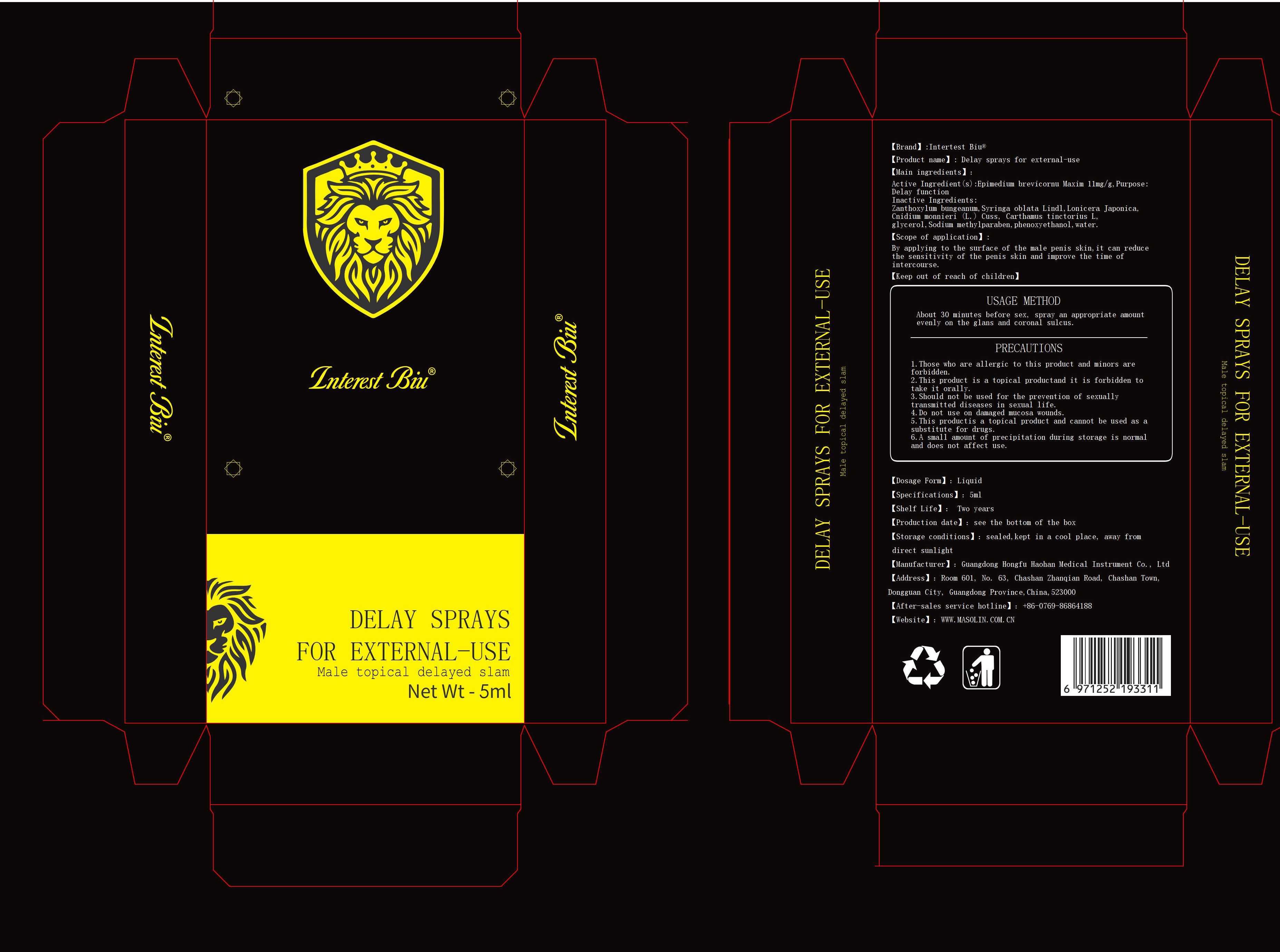 DRUG LABEL: Delay sprays for external-use
NDC: 82408-301 | Form: LIQUID
Manufacturer: Guangdong Hongfu Haohan Medical Instrument Co., Ltd.
Category: homeopathic | Type: HUMAN OTC DRUG LABEL
Date: 20211122

ACTIVE INGREDIENTS: EPIMEDIUM BREVICORNU WHOLE 0.11 g/1 g
INACTIVE INGREDIENTS: PHENOXYETHANOL; CROCIN; GLYCERIN; METHYLPARABEN; LONICERA JAPONICA FLOWER; WATER; OSTHOL; METHOXSALEN; GARDENOSIDE

Delay sprays for external-use, 5mL

Active ingredient

Epimedium Brevicornu Maxim 11% w/w

Purpose

Delay function.

Reduce the sensitivity of the penis skin and improve the time of intercourse.

Warnings

1.Those who are allergic to this product and minors are forbidden.
2.This product is a topical productand it is forbidden to take it orally.
3.Should not be used for the prevention of sexually transmitted diseases in sexual life.
4.Do not use on damaged mucosa wounds.
5.This productis a topical product and cannot be used as a substitute for drugs.
6.A small amount of precipitation during storage is normal and does not affect use.

When using

By applying to the surface of the male penis skin, about 30 minutes before sex, spray an appropriate amount evenly on the glans and coronal sulcus.

Those who are allergic to this product and minors are forbidden.
This product is a topical productand it is forbidden to take it orally.
Should not be used for the prevention of sexually transmitted diseases in sexual life.
Do not use on damaged mucosa wounds.
This productis a topical product and cannot be used as a substitute for drugs.

A small amount of precipitation during storage is normal and does not affect use.

Do not use

Those who are allergic to this product and minors are forbidden.
This product is a topical productand it is forbidden to take it orally.
Should not be used for the prevention of sexually transmitted diseases in sexual life.
Do not use on damaged mucosa wounds.
This productis a topical product and cannot be used as a substitute for drugs.

Keep out of reach of children

Scope of application

By applying to the surface of the male penis skin,it can reduce the sensitivity of the penis skin and improve the time of intercourse.

USAGE METHOD

About 30 minutes before sex, spray an appropriate amount evenly on the glans and coronal sulcus.

Inactive ingredients

Zanthoxylum bungeanum, Syringa oblata Lindl, Lonicera Japonica, Cnidium monnieri (L.) Cuss, Carthamus tinctorius L, glycerol, Sodium methylparaben, phenoxyethanol, water.

Questions

After-sales service hotline: +86-0769-86864188